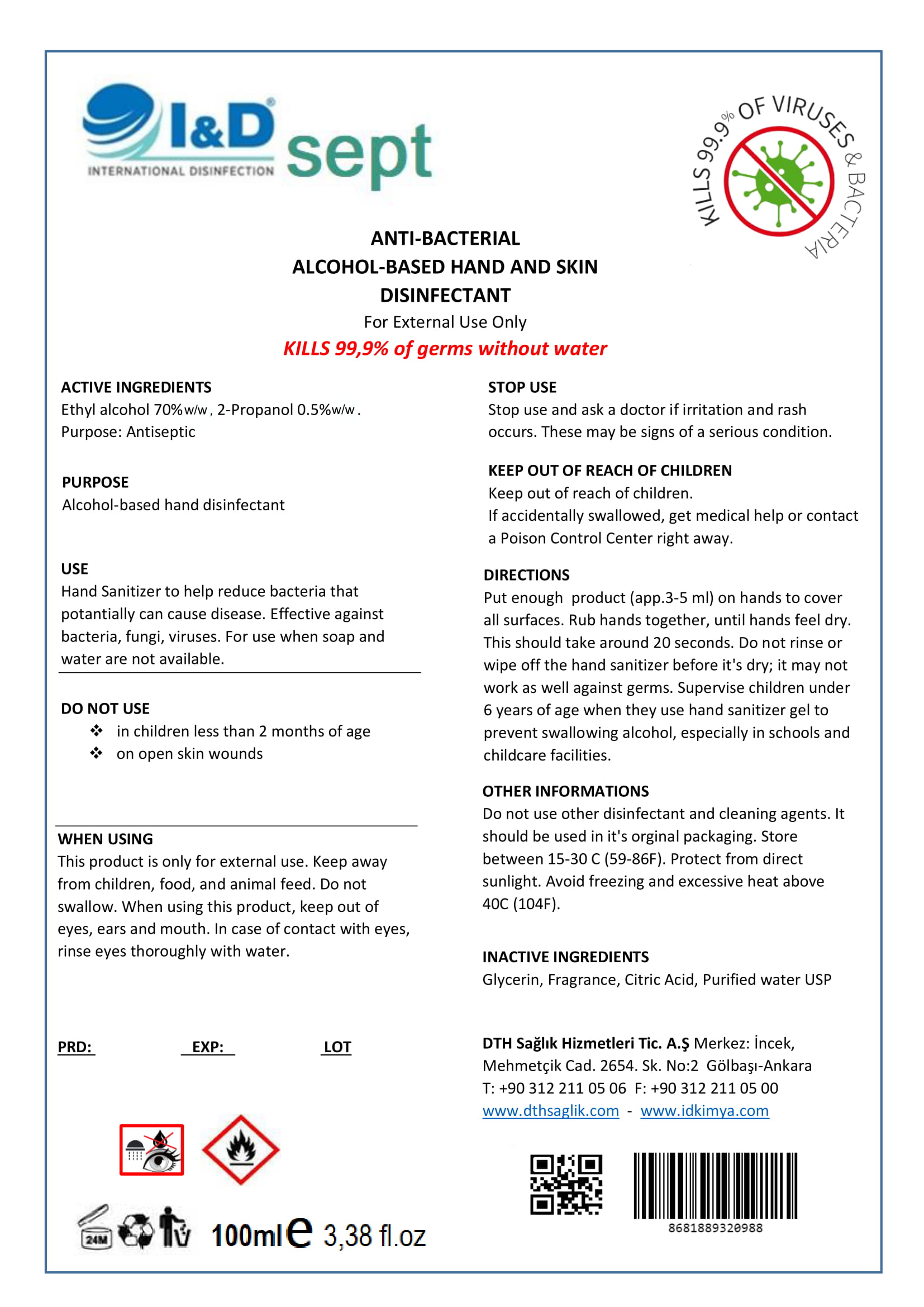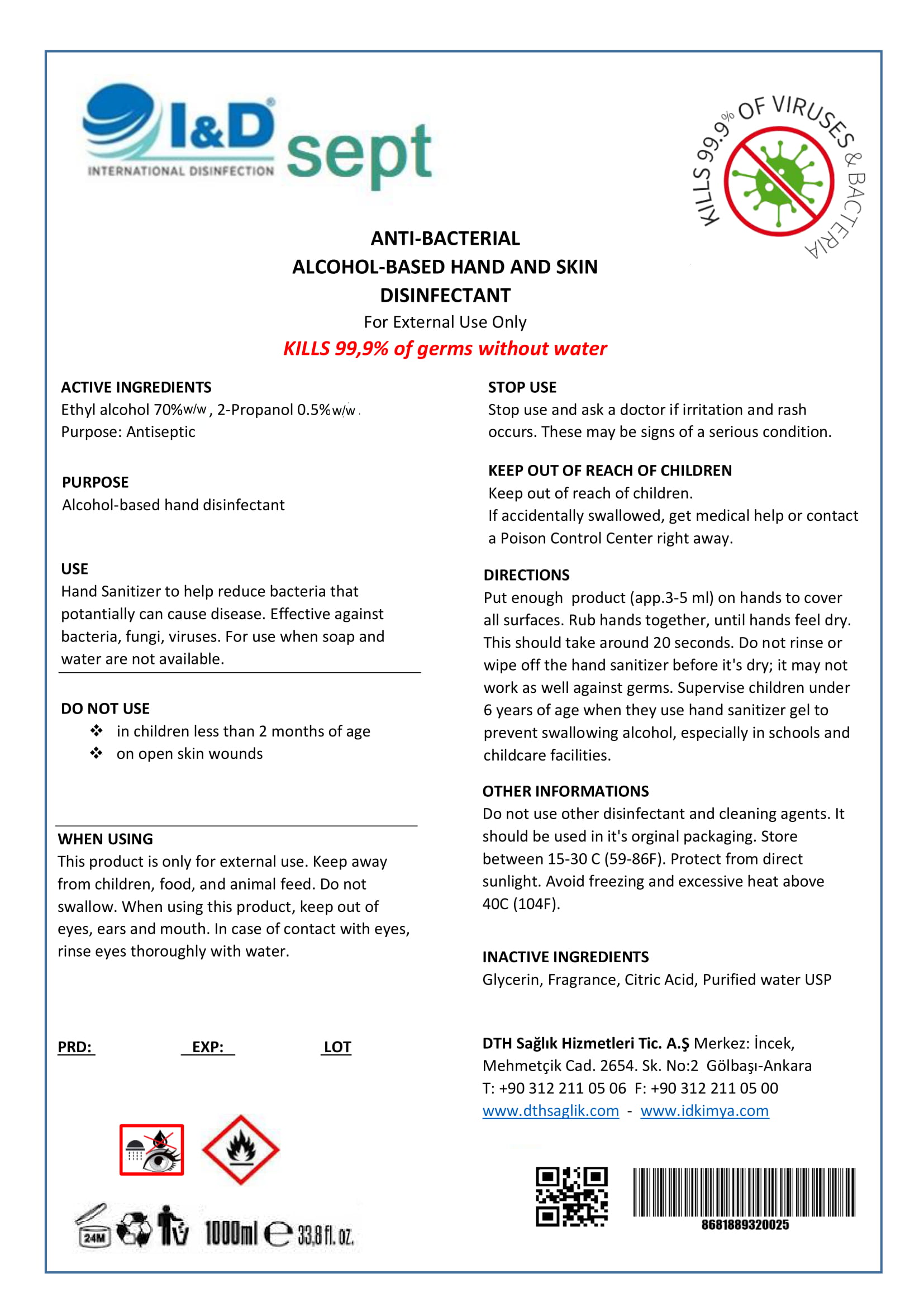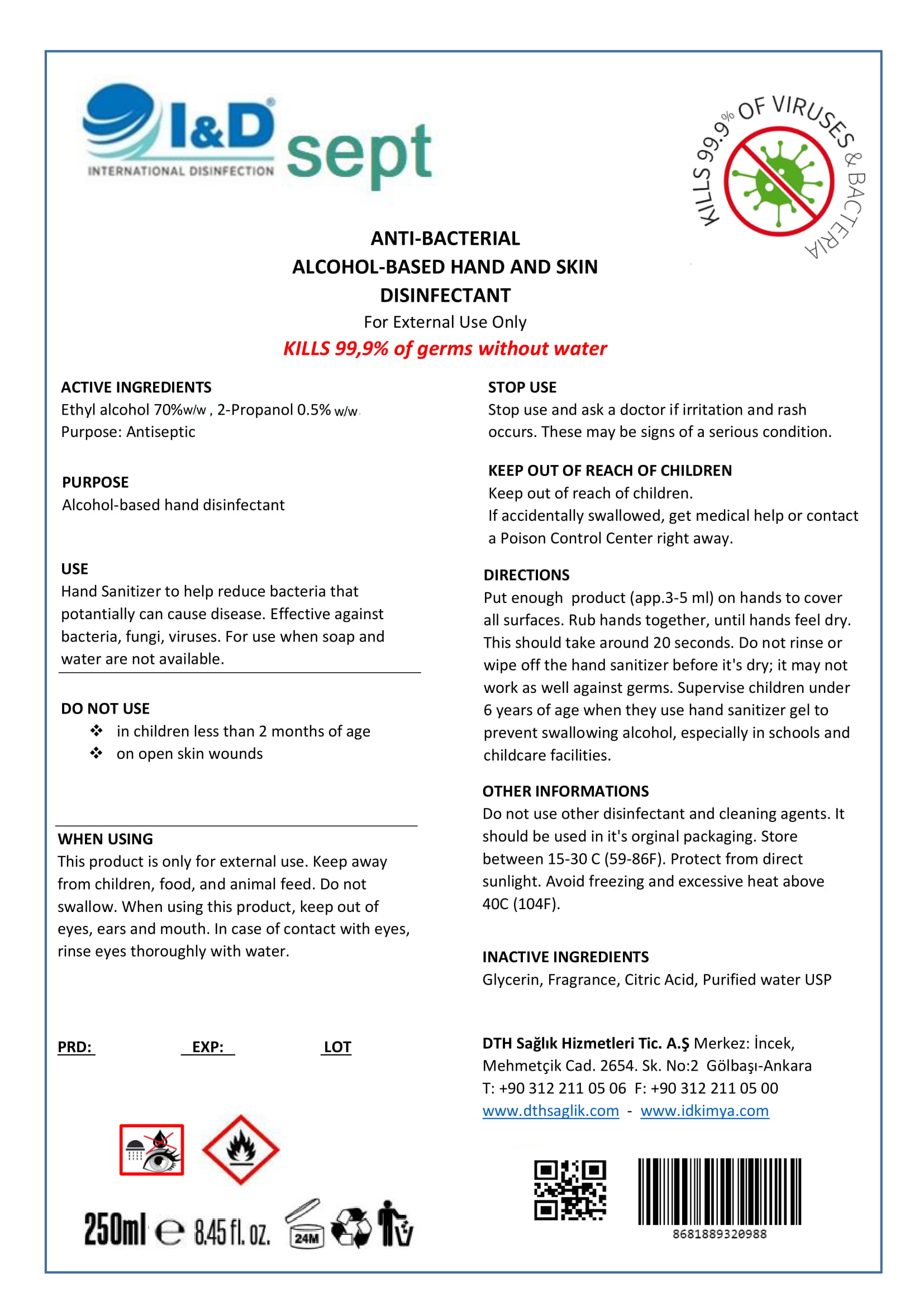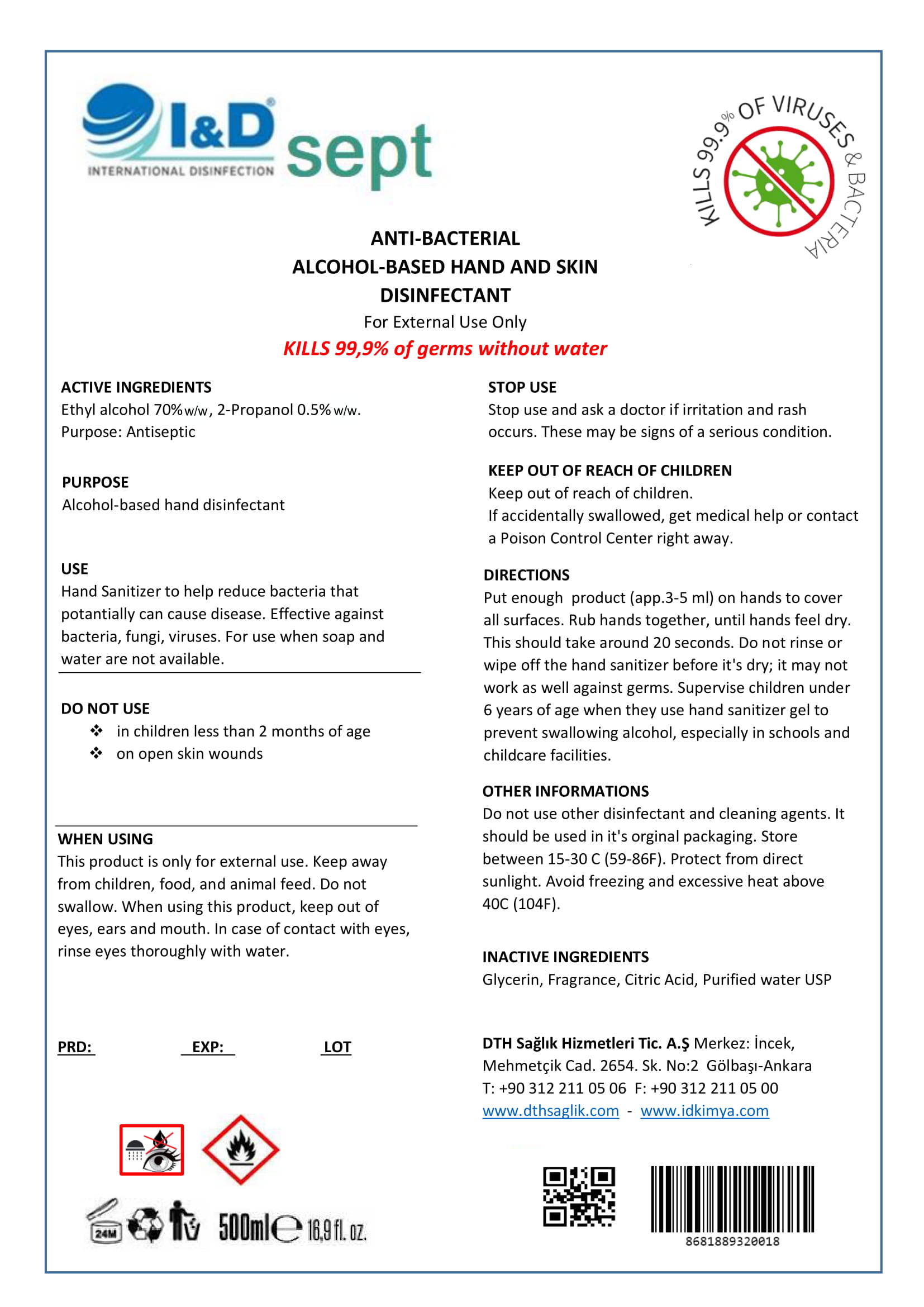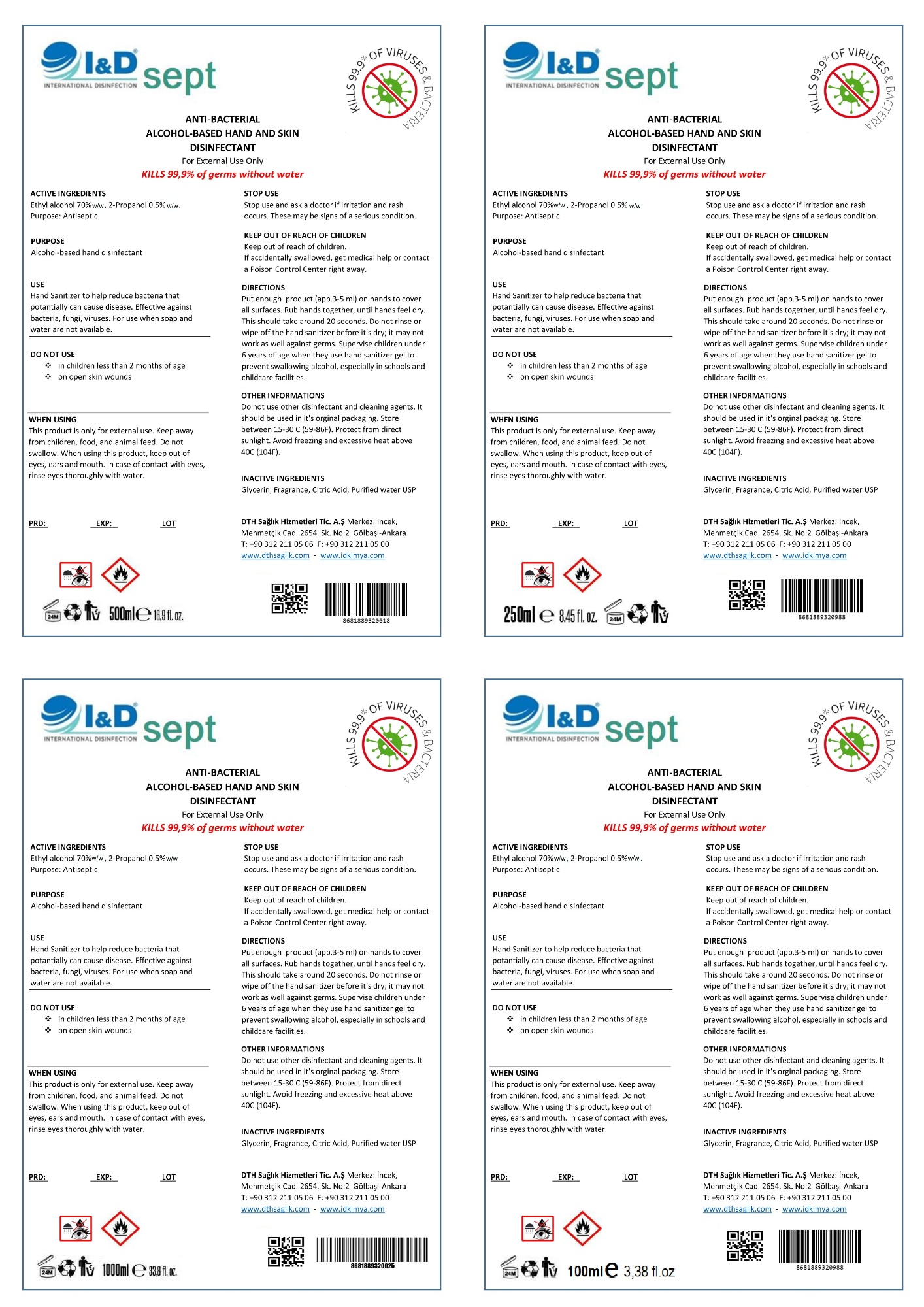 DRUG LABEL: ANTI-BACTERIAL ALCOHOL-BASED HAND AND SKIN DISINFECTANT
NDC: 78992-612 | Form: LIQUID
Manufacturer: DTH SAGLIK HIZMETLERI TICARET ANONIM SIRKETI
Category: otc | Type: HUMAN OTC DRUG LABEL
Date: 20200629

ACTIVE INGREDIENTS: ISOPROPYL ALCOHOL 0.5 mL/100 mL; ALCOHOL 70 mL/100 mL
INACTIVE INGREDIENTS: GLYCERIN; WATER; CITRIC ACID MONOHYDRATE

Hand Sanitizer Liquid

Active Ingredient(s)

Ethyl alcohol 70% w/w, 2-Propanol 0.5% w/w

Purpose

Antiseptic

Alcohol-based hand disinfectant

Use

Hand Sanitizer to help reduce bacteria that potentially can cause disease. Effective against bacteria, fungi, viruses. For use when soap and water are not available.

Warnings

This product is only for external use. Keep away from children, food, and animal feed. Do not swallow.

Do not use

- in children less than 2 months of age
- on open skin wounds

When using this product keep out of eyes, ears, and mouth. In case of contact with eyes, rinse eyes thoroughly with water.

Stop use and ask a doctor if irritation and rash occurs. These may be signs of a serious condition.

Keep out of reach of children. If swallowed, get medical help or contact a Poison Control Center right away.

Directions

Put enough product (app.3-5 ml) on hands to cover all surfaces. Rub hands together, until hands feel dry. This should take araound 20 seconds. Do not rinse or wipe off the hand sanitizer before it's dry; it may not work as well against germs.

Supervise children under 6 years of age when they use hand sanitizer gel to prevent swallowing alcohol, especially in schools and childcare facilities.

Other information

Do not use other disinfectant and cleaning agents. It should be used in it's orginal packaging. Store between 15-30 C (59-86F).Protect from direct sunlight. Avoid freezing and excessive heat above 40C (104F)

Inactive ingredients

Glycerin, Fragrance, Citric acid, Purified water USP

Package Label - Principal Display Panel

DTH Saglik Hizmetleri Tic. A.S. Merkez: Incek Mehmetcik Cad. 2654. Sk. No:2 Golbasi-Ankara

T: +90 312 211 05 06 F: +90 312 211 05 00

wwww.dthsaglik.com - www.idkimya.com

I& D sept INTERNATIONAL DISINFECTION

ANTI-BACTERIAL ALCOHOL BASED HAND AND SKIN DISINFECTANT

For External Use Only

KILLS 99,9% of germs without water

KILLS 99,9% VIRUSES & BACTERIA